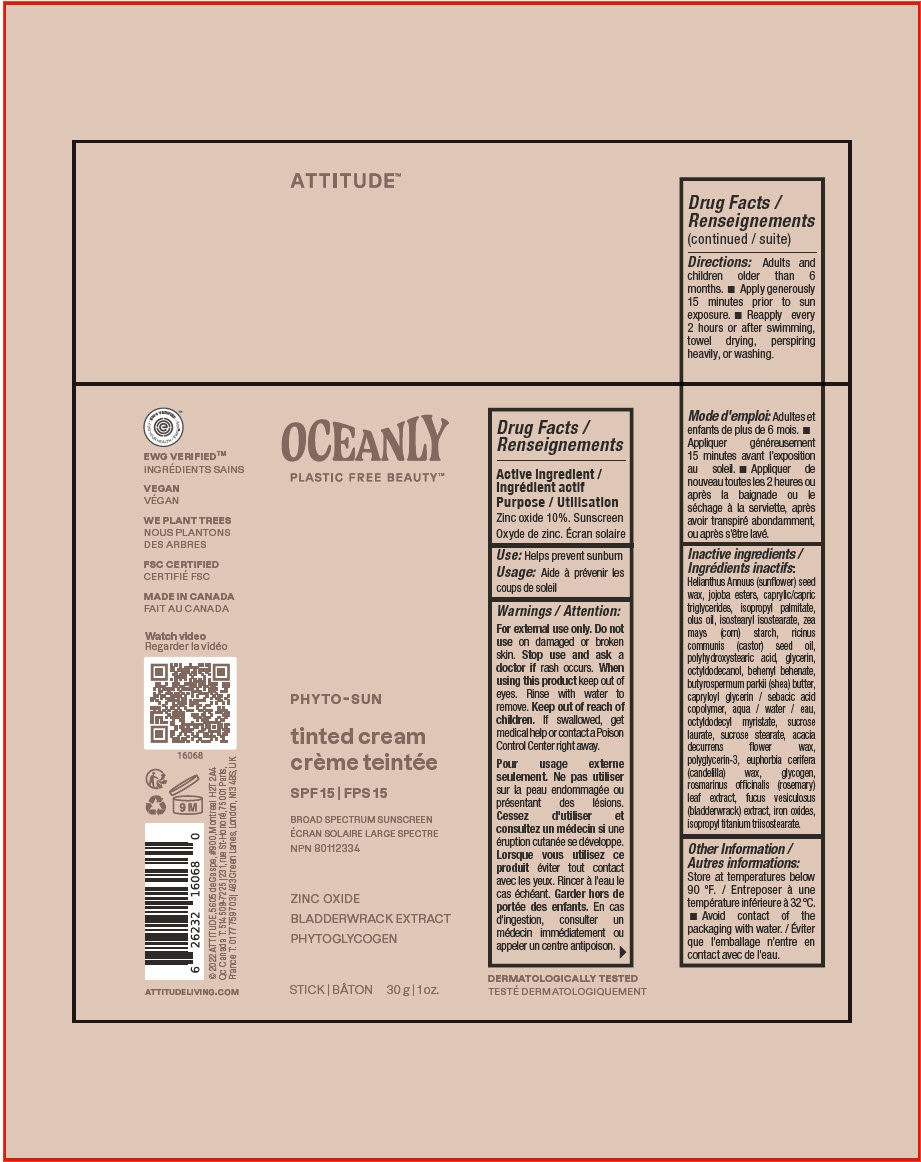 DRUG LABEL: Attitude Oceanly Phyto-Sun Tinted - SPF 15 - Broad Spectrum Sunscreen
NDC: 61649-068 | Form: STICK
Manufacturer: Attitude DBA 9055-7588 Québec Inc.
Category: otc | Type: HUMAN OTC DRUG LABEL
Date: 20251020

ACTIVE INGREDIENTS: ZINC OXIDE 10 g/100 g
INACTIVE INGREDIENTS: HELIANTHUS ANNUUS SEED WAX; POLYHYDROXYSTEARIC ACID (2300 MW); JOJOBA OIL, RANDOMIZED; MEDIUM-CHAIN TRIGLYCERIDES; ISOPROPYL PALMITATE; CORN OIL; C10-18 TRIGLYCERIDES; ISOSTEARYL ISOSTEARATE; STARCH, CORN; CASTOR OIL; SHEA BUTTER; GLYCERIN; OCTYLDODECANOL; BEHENYL BEHENATE; CAPRYLOYL GLYCERIN/SEBACIC ACID COPOLYMER (2000 MPA.S); WATER; OCTYLDODECYL MYRISTATE; SUCROSE LAURATE; SUCROSE STEARATE; ACACIA DECURRENS FLOWER WAX; POLYGLYCERIN-3; CANDELILLA WAX; GLYCOGEN; ROSEMARY; FUCUS VESICULOSUS; FERRIC OXIDE RED; FERROSOFERRIC OXIDE; FERRIC OXIDE YELLOW; ISOPROPYL TITANIUM TRIISOSTEARATE

Attitude™ Oceanly Phyto-Sun Tinted cream - SPF 15 - Broad Spectrum Sunscreen

Drug Facts

Active ingredient

Zinc oxide 10%.

Purpose

Sunscreen

Use

Helps prevent sunburn

Warnings

For external use only.

Do not useon damaged or broken skin.

Stop use and ask doctor ifrash occurs.

WHEN USING

When using this productkeep out of eyes. Rinse with water to remove.

Keep out of reach of children.If swallowed, get medical help or contact a Poison Control Center right away.

Directions

Adults and children older than 6 months.

- Apply generously 15 minutes prior to sun exposure.
- Reapply every 2 hours or after swimming, towel drying, perspiring heavily, or washing .

Inactive ingredients

Helianthus Annuus (sunflower) seed wax, jojoba esters, caprylic/capric triglycerides, isopropyl palmitate, olus oil, isostearyl isostearate, zea mays (corn) starch, ricinus communis (castor) seed oil, polyhydroxystearic acid, glycerin, octyldodecanol, behenyl behenate, butyrospermum parkii (shea) butter, capryloyl glycerin / sebacic acid copolymer, aqua / water / eau, octyldodecyl myristate, sucrose laurate, sucrose stearate, acacia decurrens flower wax, polyglycerin-3, euphorbia cerifera (candelilla) wax, glycogen, rosmarinus officinalis (rosemary) leaf extract, fucus vesiculosus (bladderwrack) extract, iron oxides, isopropyl titanium triisostearate.

Other Information

Store at temperatures below 90 °F.

- Avoid contact of the packaging with water.

PRINCIPAL DISPLAY PANEL - 30 g Tube Label

ATTITUDE™

OCEANLY
PLASTIC FREE BEAUTY™

PHYTO-SUN

tinted cream
SPF 15

BROAD SPECTRUM SUNSCREEN

NPN 80112334

ZINC OXIDE
BLADDERWRACK EXTRACT
PHYTOGLYCOGEN

STICK
30 g | 1 oz.